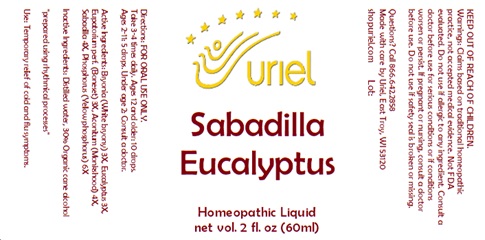 DRUG LABEL: Sabadilla Eucalyptus
NDC: 48951-8313 | Form: LIQUID
Manufacturer: Uriel Pharmacy Inc.
Category: homeopathic | Type: HUMAN OTC DRUG LABEL
Date: 20240221

ACTIVE INGREDIENTS: BRYONIA ALBA ROOT 3 [hp_X]/1 mL; EUCALYPTUS GUM 3 [hp_X]/1 mL; EUPATORIUM PERFOLIATUM FLOWERING TOP 3 [hp_X]/1 mL; ACONITUM NAPELLUS 4 [hp_X]/1 mL; SCHOENOCAULON OFFICINALE SEED 4 [hp_X]/1 mL; PHOSPHORUS 6 [hp_X]/1 mL
INACTIVE INGREDIENTS: WATER; ALCOHOL

Sabadilla Eucalyptus

DOSAGE AND ADMINISTRATION

Take 3-4 times daily. Ages 12 and older: 10 drops. Ages 2-11: 5 drops. Under age 2: Consult a doctor

ACTIVE INGREDIENT

Active Ingredients: Bryonia (White bryony) 3X, Eucalyptus 3X, Eupatorium perf. (Boneset) 3X, Aconitum (Monkshood) 4X, Sabadilla 4X, Phosphorus (Yellow phosphorus) 6X

Inactive Ingredients: Distilled water, Organic cane alcohol

"prepared using rhythmical processes"

PURPOSE

Use: Temporary relief of cold and flu symptoms.

KEEP OUT OF REACH OF CHILDREN.

WARNINGS

Warnings: Claims based on traditional homeopathic practice, not accepted medical evidence. Not FDA evaluated. Do not use if allergic to any ingredient. Consult a doctor before use for serious conditions or if conditions worsen or persist. If pregnant or nursing, consult a doctor before use. Do not use if safety seal is broken or missing.

QUESTIONS

Questions? Call 866.642.2858 Made with care by Uriel, East Troy, WI 53120 shopuriel.com Lot: